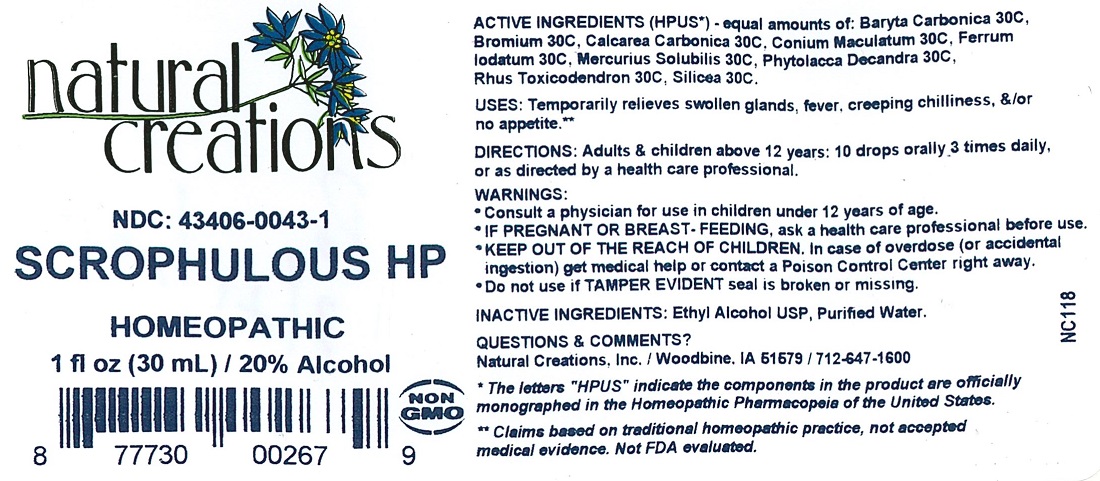 DRUG LABEL: SCROPHULOUS HP
NDC: 43406-0043 | Form: LIQUID
Manufacturer: Natural Creations, Inc.
Category: homeopathic | Type: HUMAN OTC DRUG LABEL
Date: 20251216

ACTIVE INGREDIENTS: BARIUM CARBONATE 30 [hp_C]/1 mL; BROMINE 30 [hp_C]/1 mL; OYSTER SHELL CALCIUM CARBONATE, CRUDE 30 [hp_C]/1 mL; CONIUM MACULATUM FLOWERING TOP 30 [hp_C]/1 mL; FERROUS IODIDE 30 [hp_C]/1 mL; MERCURIUS SOLUBILIS 30 [hp_C]/1 mL; PHYTOLACCA AMERICANA ROOT 30 [hp_C]/1 mL; TOXICODENDRON PUBESCENS LEAF 30 [hp_C]/1 mL; SILICON DIOXIDE 30 [hp_C]/1 mL
INACTIVE INGREDIENTS: WATER; ALCOHOL

SCROPHULOUS HP

ACTIVE INGREDIENT

ACTIVE INGREDIENTS (HPUS*) equal amounts of: Baryta Carbonica 30C, Bromium 30C, Calcarea Carbonicum 30C, Conium Maculatum 30C, Ferrum Iodatum 30C, Mercurius Solubilis 30C, Phytolacca Decandra 30C, Rhus Toxicodendron 30C, Silicea 30C

PURPOSE

USES: Temporarily relieves swollen glands, fever, creeping chilliness, &/or no appetite.**

INDICATIONS AND USAGE

USES: Temporarily relieves swollen glands, fever, creeping chilliness, &/or no appetite.**

DOSAGE AND ADMINISTRATION

Directions: Adults & children above 12 years: 10 drops orally 3 times daily, or as directed by a health care professional.

KEEP OUT OF REACH OF CHILDREN

* KEEP OUT OF THE REACH OF CHILDREN. In case of overdose (or accidental ingestion) get medical help or contact a Poison Control Center right away.

WARNINGS:

- Consult a physician for use in children under 12 years of age.
- IF PREGNANT OR BREAST-FEEDING, ask a health care professional before use.
- KEEP OUT OF THE REACH OF CHILDREN. In case of overdose (or accidental ingestion) get medical help or contact a Poison Control Center right away.
- Do not use if TAMPER EVIDENT seal is broken or missing.

Inactive Ingredients: Ethyl Alcohol USP, Purified Water.

QUESTIONS

Questions & Comments? Natural Creations, Inc. / Woodbine, IA 51579 / 712-647-1600

REFERENCES

*The letters “HPUS” indicate the components in the product are officially monographed in the Homeopathic Pharmacopeia of the United States.

** Claims based on traditional homeopathic practice, not accepted medical evidence. Not FDA evaluated.

PACKAGE LABEL

NDC: 43406-0043-1

SCROPHULOUS HP

HOMEOPATHIC

1 fl oz (30 mL) 20% Alcohol